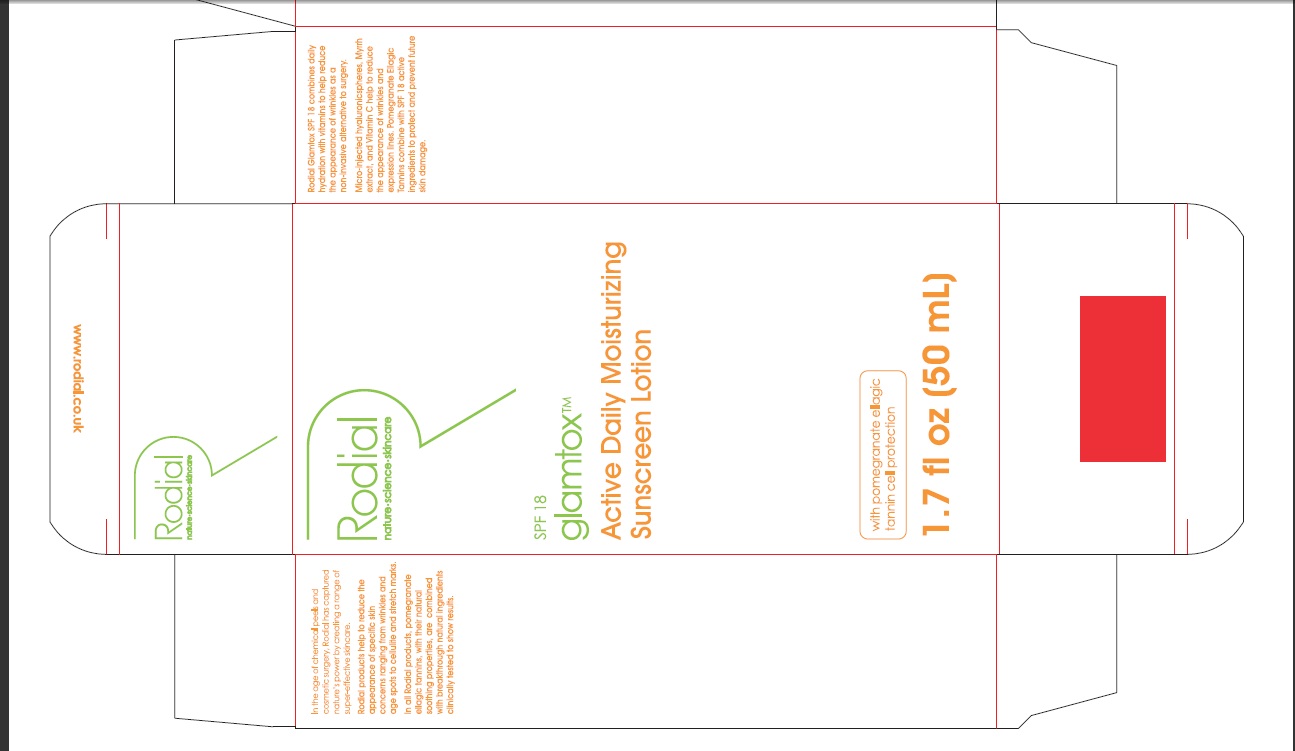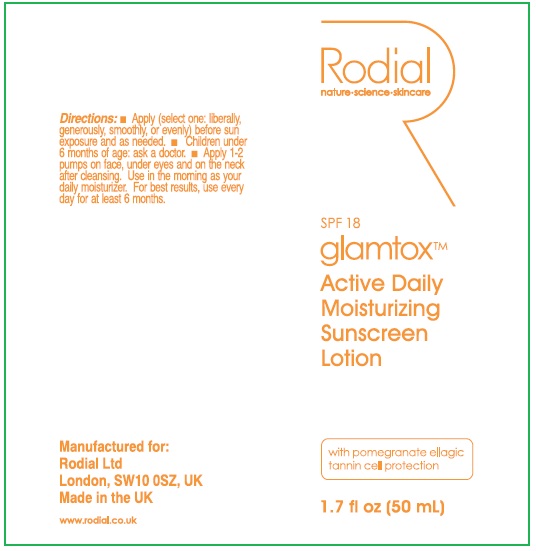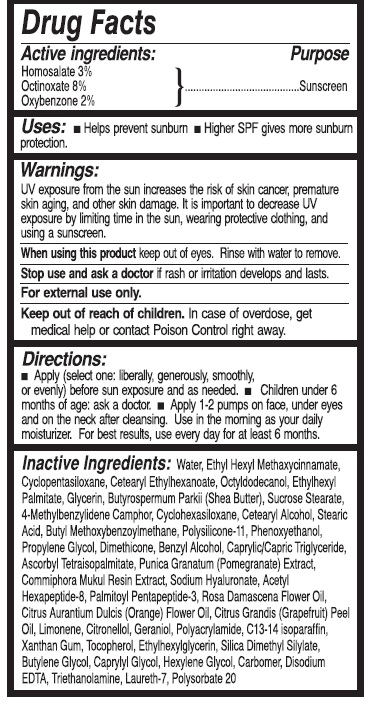 DRUG LABEL: GLAMTOX ACTIVE DAILY MOISTURIZING SUNSCREEN
NDC: 52456-018 | Form: LIQUID
Manufacturer: Rodial, Ltd.
Category: otc | Type: HUMAN OTC DRUG LABEL
Date: 20100706

ACTIVE INGREDIENTS: HOMOSALATE 3 mL/100 mL; OCTINOXATE 8 mL/100 mL; OXYBENZONE 2 mL/100 mL

SPF 18 GLAMTOX ACTIVE DAILY MOISTURIZING SUNSCREEN LOTION

DRUG FACTS

Active Ingredients Purpose

Homosalate Sunscreen

Octinoxate Sunscreen

Oxybenzone Sunscreen

PURPOSE

Uses: Helps prevent sunburn

Higher SPF gives more sunburn protection

WARNINGS

UV exposure from the sun increases the risk of skin cancer, premature skin aging and other skin damage. It is important to decrease UV exposure by limiting time in the sun, wearing protective clothing, and using a sunscreen.

When using this product keep out of eyes. Rinse with water to remove.

Stop use and ask a doctor if rash or irritation develops and lasts.

For external use only.

Keep out of reach of children. In case of overdose, get medical help or contact Poison control right away.

DOSAGE AND ADMINISTRATION

Directions: Apply (select one: liberally, generously, smoothly, or evenly) before sun exposure and as needed.

Children under 6 months of age ask a doctor

Apply 1-2 pumps on face, under eyes and on the neck after cleansing. Use in the morning as your daily moisturizer. For best results use everyday for at least 6 months.

INDICATIONS AND USAGE

Inactive Ingredients:

Water, Ethyl Hexyl Methaxycinnamate, Cyclopentasiloxane, cetearyl ethylhexanoate, octyldodecanon, ethylhexyl palmitate, glycerin, butysprmum parkii (Shea butter), sucrose stearate, 4-methylbenzylidene camphor, cyclohexasiloxane, cetearyl alcohol, stearic acid, butyl methoxybenzoylmethane, polysilicone-11, phenoxyethanol, propylene glycol, dimethicone, benzyl alcohol, caprylic/capric triglyceride, ascorbyl tetraisopalmitate, punica granatum (pomegranate) extract, commiphora mukul resin extract, sodium hyaluronate, acetyl hexapeptide-8, palmitoyl pentapeptide-3, rosa damascena flower oil, citrus aurantium dulcis (orange) flower oil, citrus grandis (grapefruit) peel oil, Limonene, citronellol, geraniol, polyacrylamide, c13-14 isoparaffin xanthan gum,, tocopherol, ethylhexylglycerin, silica dimethyl silylate, butylene glycol, caprylyl glycol, hexylene glycol, carbomer, disodium EDTA, triethanolamine, laureth-7, polysorbate 20

In the age of chemical peels and cosmetic surgery, Rodial has captured natures power by creating a range of supper effective skincare.

Rodial products help to reduce the appearance of specific skin concerns from wrinkles and age spots to cellulite and stretch marks.

In all Rodial products, pomegranate ellagic tannins, with their natural soothing properties are combined with breakthrough natural ingredients clinically tested to show results.

PACKAGE LABEL

SPF 18

Glamtox

Active Daily Moisturizing Sunscreen Lotion

with pomegranate ellagic tannin cell protection

1.7 fl. oz. (50 ml)

Rodial Glamtox SPF 18 combines daily hydration with vitamins to help reduce the appearance of wrinkles as a non-invasive alternative to surgery.

Micro-injected hyaluronicspheres, Myrrh extract, and Vitamin C help to reduce the appearance of wrinkes and expression lines. Pomegranate Ellagic Tannins combine with SPF 18 active ingredients to protect and prevent future skin damage.

Directions

Apply (select one: liberally, generously, smoothly or evenly) before sun exposure and as needed.

Children under 6 months of age: ask a doctor

Apply 1-2 pumps on face, under eyes and on the neck after cleansing. Use in the morning as your daily moisturizer. for best results, user every day for at least 6 months.

Manufactured for

Rodial Ltd.

London, SW10 0SZ, UK

Made in the UK

www.rodial.co.uk

SPF 18

Glamtox

Active Daily Moisturizing Sunscreen Lotion

with pomegranate ellagic tannin cell protection

1.5 fl oz. (50 ml)